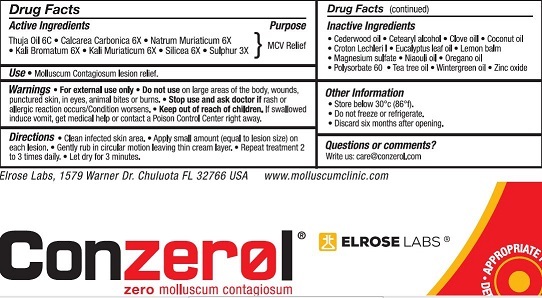 DRUG LABEL: Elroselabs
NDC: 70223-001 | Form: CREAM
Manufacturer: Elroselabs Inc.
Category: homeopathic | Type: HUMAN OTC DRUG LABEL
Date: 20151116

ACTIVE INGREDIENTS: POTASSIUM CHLORIDE 6 [hp_X]/30 g; SULFUR 3 [hp_X]/30 g; POTASSIUM BROMIDE 6 [hp_X]/30 g; SILICON DIOXIDE 6 [hp_C]/30 g; OYSTER SHELL CALCIUM CARBONATE, CRUDE 6 [hp_C]/30 g; SODIUM CHLORIDE 6 [hp_X]/30 g
INACTIVE INGREDIENTS: MAGNESIUM SULFATE, UNSPECIFIED; METHYL SALICYLATE; CLOVE OIL; CEDRUS ATLANTICA BARK OIL; OREGANO LEAF OIL; NIAOULI OIL; COCONUT OIL; WHITE WAX; POLYSORBATE 60; GLYCERIN; ZINC OXIDE; TEA TREE OIL; MELISSA OFFICINALIS; CROTON LECHLERI RESIN; EUCALYPTUS CAMALDULENSIS LEAF OIL

PURPOSE

Topical Use for

Homeopathic treatment for Molluscum Contagiosum

ACTIVE INGREDIENTS

SILICEA

CALCAREA CARBONICA

THUJA OIL

NATRUM MURIATICUM

KALI BROMATUM

SULPHUR

KALI MURIATICUM

INACTIVE INGREDIENT

CROTON LECHLERI RESIN
EMULSIFYING WAX NF
POLYSORBATE 60
MAGNESIUM SULFATE, UNSPECIFIED
VEGETABLE GLYCERIN
ZINC OXIDE
DIMETHYL ISOSORBIDE
TEA TREE OIL
METHYL SALICYLATE
CLOVE OIL
MELISSA OFFICINALIS
OREGANO LEAF OIL
CEDRUS ATLANTICA BARK OIL
NIAOULI OIL
EUCALYPTUS CAMALDULENSIS LEAF OIL
COCONUT OIL

DIRECTIONS

Clean infected skin area'.

Apply small amount (equal to lesion size) on each lesion.

Gently rub in circular motion leaving thin cream layer.

Repeat treatment 2 to 3 times daily.

Let dry for 3 minutes.

USE

Molluscum Contagiosum lesion relief.

WARNINGS

For external use only. Do not use on large areas of the body, wounds, punctured skin, in eyes or animal bites or burns.

Stop use and ask doctor if rash or allergic reaction occurs / condition worsens.

KEEP OUT OF REACH OF CHILDREN.

If swallowed induce vomit.

OTHER SAFETY INFORMATION

Store below 30°c (86°f)

Do not freeze or refrigerate.

Discard 6 month after opening.